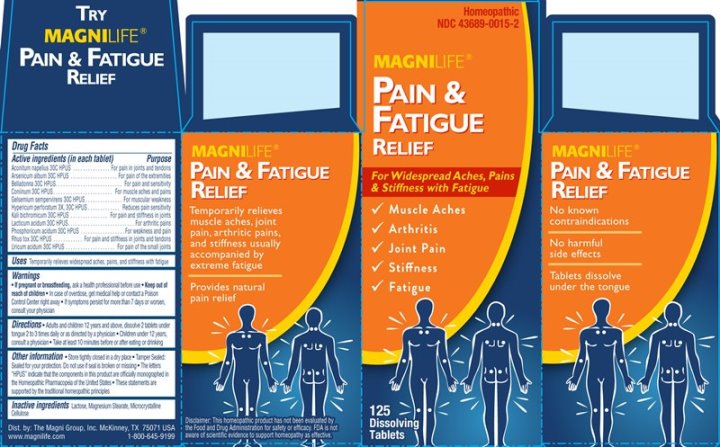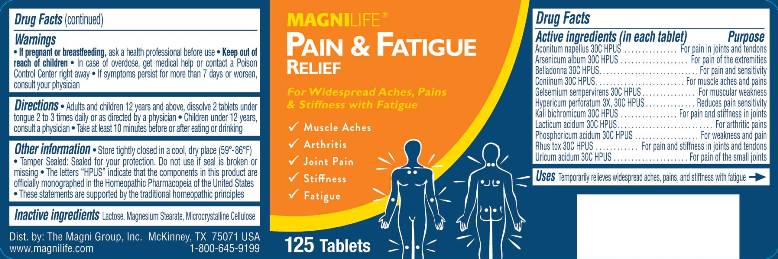 DRUG LABEL: Pain and Fatigue Relief
NDC: 43689-0015 | Form: TABLET
Manufacturer: The Magni Company
Category: homeopathic | Type: HUMAN OTC DRUG LABEL
Date: 20230126

ACTIVE INGREDIENTS: ACONITUM NAPELLUS WHOLE 30 [hp_C]/1 1; ARSENIC TRIOXIDE 30 [hp_C]/1 1; ATROPA BELLADONNA 30 [hp_C]/1 1; CONIINE 30 [hp_C]/1 1; GELSEMIUM SEMPERVIRENS ROOT 30 [hp_C]/1 1; HYPERICUM PERFORATUM WHOLE 3 [hp_X]/1 1; POTASSIUM DICHROMATE 30 [hp_C]/1 1; LACTIC ACID, DL- 30 [hp_C]/1 1; PHOSPHORIC ACID 30 [hp_C]/1 1; TOXICODENDRON PUBESCENS LEAF 30 [hp_C]/1 1; URIC ACID 30 [hp_C]/1 1
INACTIVE INGREDIENTS: LACTOSE; MAGNESIUM STEARATE; CELLULOSE, MICROCRYSTALLINE

DRUG FACTS:

ACTIVE INGREDIENTS:

Aconitum Napellus 30C, Arsenicum Album 30C, Belladonna 30C, Coniinum 30C, Gelsemium Sempervirens 30C, Hypericum Perforatum 3X, 30C, Kali Bichromicum 30C, Lacticum Acidum 30C, Phosphoricum Acidum 30C, Rhus Tox 30C, Uricum Acidum 30C

INDICATIONS:

Temporarily relieves widespread aches, pains, and stiffness with fatigue

WARNINGS:

• If pregnant or breastfeeding, ask a health professional before use

• Keep out of reach of children. In case of overdose, get medical help or contact a Poison Control Center right away

• If symptoms persist for more than 7 days or worsen, consult your physician

OTHER INFORMATION:

• Store tightly closed in a cool, dry place.

• Tamper sealed: Sealed for your protection. Do not use if seal is broken or missing

• The letters "HPUS" indicate that the components in this product are officially monographed in the Homeopathic Pharmacopeia of the United

States

• These statements are supported by the traditional homeopathic principles

DIRECTIONS:

• Adults and children 12 years and above: Dissolve 2 tablets under tongue 2 to 3 times daily or as directed by a physician

• Children under 12: Consult a physician

• Take at least 10 minutes before or after eating or drinking

INACTIVE INGREDIENTS:

Lactose, Magnesium Stearate, Microcrystalline Cellulose

Keep out of reach of children. In case of overdose, get medical help or contact a Poison Control Center right away

INDICATIONS:

Temporarily relieves widespread aches, pains, and stiffness with fatigue

QUESTIONS:

Dist. by: The Magni Group, Inc. McKinney, TX 75071 USA

www.magilife.com 1-800-645-9199

PACKAGE LABEL DISPLAY:

MAGNILIFE
PAIN & FATIGUE
RELIEF

For Widespread Aches, Pains
& Stiffness with Fatigue

√ Muscle Aches
√ Arthritis
√ Joint Pain
√ Stiffness
√ Fatigue

125 Tablets